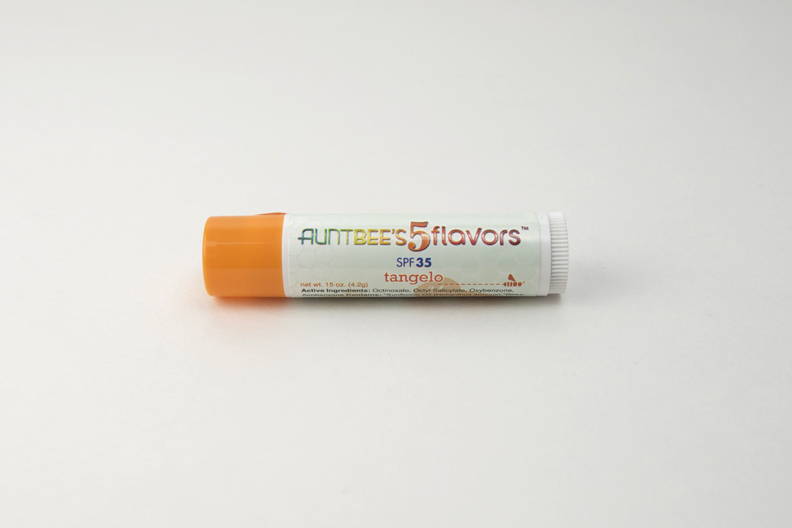 DRUG LABEL: Aunt Bees Five Flavors
NDC: 62932-145 | Form: SALVE
Manufacturer: Private Label Select
Category: otc | Type: HUMAN OTC DRUG LABEL
Date: 20150312

ACTIVE INGREDIENTS: OCTINOXATE 75 g/1000 g; OCTISALATE 50 g/1000 g; OXYBENZONE 40 g/1000 g; AVOBENZONE 10 g/1000 g
INACTIVE INGREDIENTS: Yellow Wax

Label Data

ACTIVE INGREDIENT

Active Ingredients: Octinoxate, Octyl Salicylate, Oxybenzone, Avobenzone.

INACTIVE INGREDIENT

Contains: *Sunflower Oil (Helianthus annuus), *Beeswax (Cera alba), *Jojoba Oil (Simmondsia chimensis), *Flavors, Tocopherol (non GMO), *Aloe Vera (Aloe barbadensis) *Organic

PACKAGE LABEL

Aunt Bee's5flavors tm

(flavor) balm

net wt. 15 oz (4.2g)

Made in USA in a Certified Organic facility (NM Organic Commodity Commission)

PO Box 2678 Ranchos de Taos NM 87557

www.auntbeesskincare.com 1.888.BEE.BALM

5-80189-00100-6 (UPC)